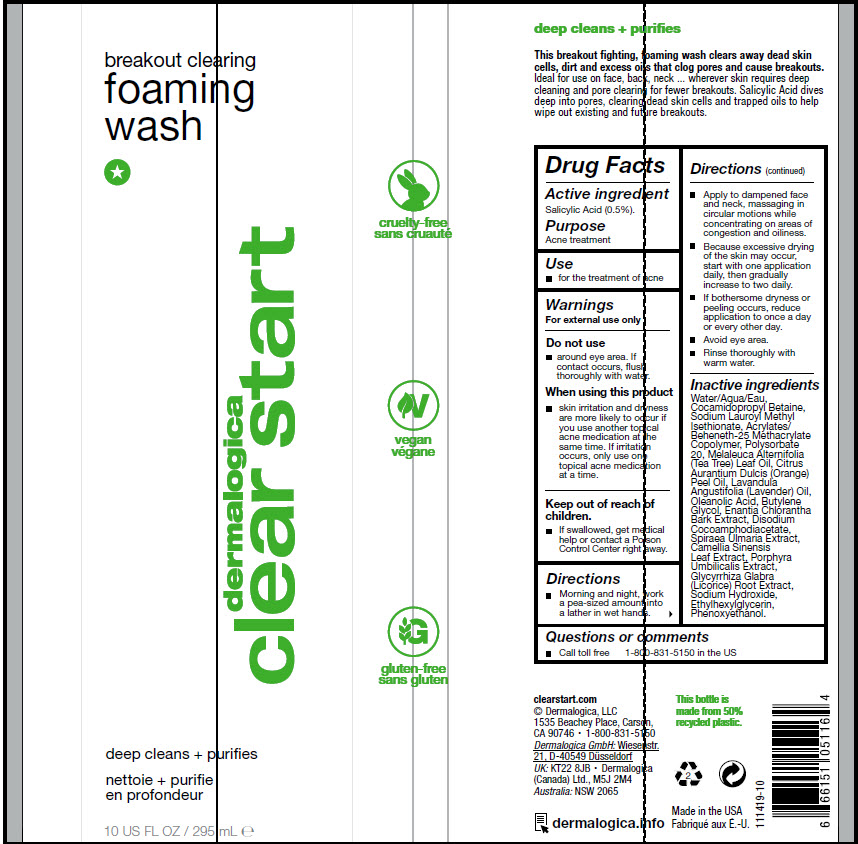 DRUG LABEL: Breakout Clearing Foaming Wash
NDC: 68479-101 | Form: LIQUID
Manufacturer: Dermalogica
Category: otc | Type: HUMAN OTC DRUG LABEL
Date: 20241224

ACTIVE INGREDIENTS: Salicylic Acid 5 mg/1 mL
INACTIVE INGREDIENTS: WATER; COCAMIDOPROPYL BETAINE; SODIUM LAUROYL METHYL ISETHIONATE; POLYSORBATE 20; TEA TREE OIL; ORANGE OIL, COLD PRESSED; LAVENDER OIL; OLEANOLIC ACID; BUTYLENE GLYCOL; ANNICKIA CHLORANTHA BARK; DISODIUM COCOAMPHODIACETATE; FILIPENDULA ULMARIA ROOT; GREEN TEA LEAF; PORPHYRA UMBILICALIS; GLYCYRRHIZA GLABRA; SODIUM HYDROXIDE; ETHYLHEXYLGLYCERIN; PHENOXYETHANOL

Breakout Clearing Foaming Wash

Drug Facts

Active ingredient

Salicylic Acid (0.5%).

Purpose

Acne treatment

Use

- for the treatment of acne

Warnings

For external use only

Do not use

- around eye area. If contact occurs, flush thoroughly with water.

When using this product

- skin irritation and dryness are more likely to occur if you use another topical acne medication at the same time. If irritation occurs, only use one topical acne medication at a time.

Keep out of reach of children.

- If swallowed, get medical help or contact a Poison Control Center right away.

Directions

- Morning and night, work a pea-sized amount into a lather in wet hands.
- Apply to dampened face and neck, massaging in circular motions while concentrating on areas of congestion and oiliness.
- Because excessive drying of the skin may occur, start with one application daily, then gradually increase to two daily.
- If bothersome dryness or peeling occurs, reduce application to once a day or every other day.
- Avoid eye area.
- Rinse thoroughly with warm water.

Inactive ingredients

Water/Aqua/Eau, Cocamidopropyl Betaine, Sodium Lauroyl Methyl Isethionate, Acrylates/Beheneth-25 Methacrylate Copolymer, Polysorbate 20, Melaleuca Alternifolia (Tea Tree) Leaf Oil, Citrus Aurantium Dulcis (Orange) Peel Oil, Lavandula Angustifolia (Lavender) Oil, Oleanolic Acid, Butylene Glycol, Enantia Chlorantha Bark Extract, Disodium Cocoamphodiacetate, Spiraea Ulmaria Extract, Camellia Sinensis Leaf Extract, Porphyra Umbilicalis Extract, Glycyrrhiza Glabra (Licorice) Root Extract, Sodium Hydroxide, Ethylhexylglycerin, Phenoxyethanol.

Questions or comments

- Call toll free 1-800-831-5150 in the US

PRINCIPAL DISPLAY PANEL - 295 mL Bottle Label

breakout clearing
foaming
wash

dermalogica
clear start

deep cleans + purifies

10 US FL OZ / 295 mL ℮